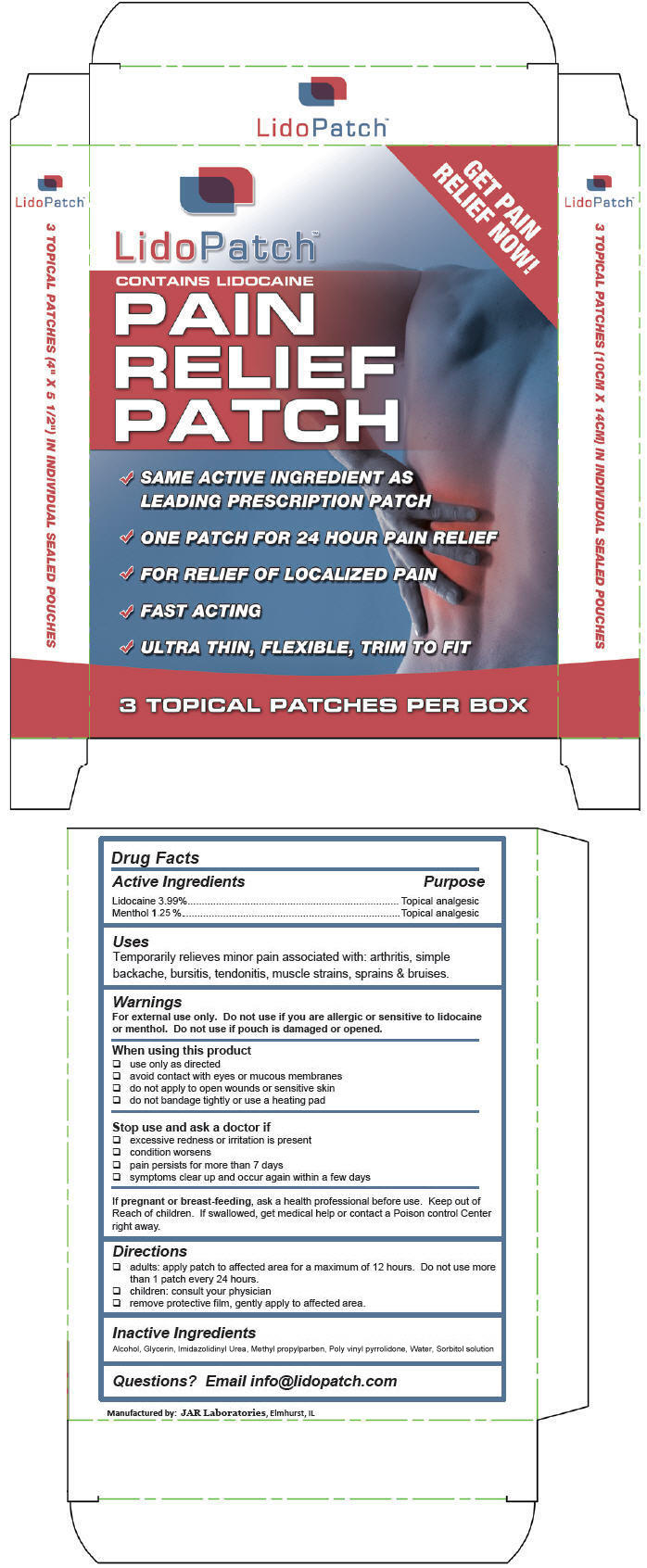 DRUG LABEL: LidoPatch
NDC: 10882-527 | Form: PATCH
Manufacturer: JAR Laboratories
Category: otc | Type: HUMAN OTC DRUG LABEL
Date: 20140130

ACTIVE INGREDIENTS: lidocaine 40 mg/1 1; menthol 50 mg/1 1
INACTIVE INGREDIENTS: GLYCERIN; COPOVIDONE K25-31; IMIDUREA; PROPYLPARABEN; ALCOHOL; SORBITOL; WATER

LidoPatch™

Drug Facts

ACTIVE INGREDIENT

Active Ingredients | Purpose
Lidocaine 3.99% | Topical analgesic
Menthol 1.25% | Topical analgesic

Uses

Temporarily relieves minor pain associated with: arthritis, simple backache, bursitis, tendonitis, muscle strains, sprains & bruises.

Warnings

For external use only.

Do not use if you are allergic or sensitive to lidocaine or menthol. Do not use if pouch is damaged or opened.

When using this product

❏ use only as directed
❏ avoid contact with eyes or mucous membranes
❏ do not apply to open wounds or sensitive skin
❏ do not bandage tightly or use a heating pad

Stop use and ask a doctor if

❏ excessive redness or irritation is present
❏ condition worsens
❏ pain persists for more than 7 days
❏ symptoms clear up and occur again within a few days

PREGNANCY OR BREAST FEEDING

If pregnant or breast-feeding, ask a health professional before use.

Keep out of Reach of children. If swallowed, get medical help or contact a Poison control Center right away.

Directions

❏ adults: apply patch to affected area for a maximum of 12 hours. Do not use more than 1 patch every 24 hours.
❏ children: consult your physician
❏ remove protective film, gently apply to affected area.

Inactive Ingredients

Alcohol, Glycerin, Imidazolidinyl Urea, Methyl propylparben, (Poly) vinyl pyrrolidone, Water, Sorbitol solution

Questions?

Email info@lidopatch.com

Manufactured by: JAR Laboratories, Elmhurst, IL

PRINCIPAL DISPLAY PANEL - 3 Topical Patch Carton

GET PAIN
RELIEF NOW!

LidoPatch™

CONTAINS LIDOCAINE
PAIN
RELIEF
PATCH

✔ ONE PATCH FOR 24 HOUR PAIN RELIEF
✔ FOR RELIEF OF LOCALIZED PAIN
✔ FAST ACTING
✔ ULTRA THIN, FLEXIBLE, TRIM TO FIT

3 TOPICAL PATCHES PER BOX